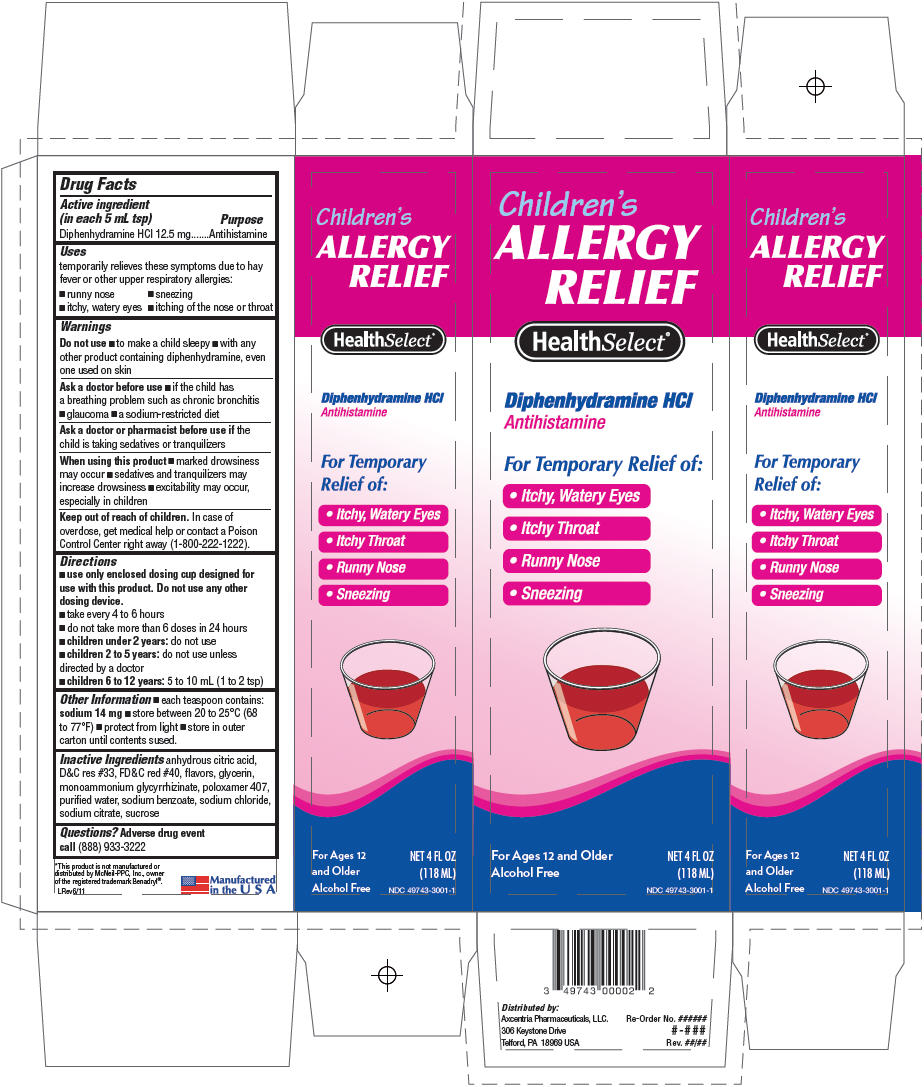 DRUG LABEL: Select Health Allergy Relief 
NDC: 49743-3003 | Form: LIQUID
Manufacturer: Axcentria Pharmaceuticals, LLC.
Category: otc | Type: HUMAN OTC DRUG LABEL
Date: 20110826

ACTIVE INGREDIENTS: Diphenhydramine Hydrochloride 12.5 mg/5 mL
INACTIVE INGREDIENTS: Citric Acid Monohydrate; Sodium Benzoate; Glycerin; polyethylene glycols; sodium citrate; sodium chloride

Children's
ALLERGY
RELIEF

Drug Facts

Active ingredient (in each 5 mL tsp)

Diphenhydramine HCl 12.5 mg

Purpose

Antihistamine

Uses

temporarily relieves these symptoms due to hay fever or other upper respiratory allergies:

- runny nose
- sneezing
- itchy, watery eyes
- itching of the nose or throat

Warnings

Do not use

- to make a child sleepy
- with any other product containing diphenhydramine, even one used on skin

Ask a doctor before use

- if the child has a breathing problem such as chronic bronchitis
- glaucoma
- a sodium-restricted diet

Ask a doctor or pharmacist before use if the child is taking sedatives or tranquilizers

When using this product

- marked drowsiness may occur
- sedatives and tranquilizers may increase drowsiness
- excitability may occur, especially in children

Keep out of reach of children. In case of overdose, get medical help or contact a Poison Control Center right away (1-800-222-1222).

Directions

- use only enclosed dosing cup designed for use with this product. Do not use any other dosing device.
- take every 4 to 6 hours
- do not take more than 6 doses in 24 hours
- children under 2 years: do not use
- children 2 to 5 years: do not use unless directed by a doctor
- children 6 to 12 years: 5 to 10 mL (1 to 2 tsp)

Other Information

- each teaspoon contains: sodium 14 mg
- store between 20 to 25°C (68 to 77°F)
- protect from light
- store in outer carton until contents sused.

Inactive Ingredients

anhydrous citric acid, D&C res #33, FD&C red #40, flavors, glycerin, monoammonium glycyrrhizinate, poloxamer 407, purified water, sodium benzoate, sodium chloride, sodium citrate, sucrose

Questions?

Adverse drug event call (888) 933-3222

PRINCIPAL DISPLAY PANEL - 118 ML Bottle Carton

Children's
ALLERGY
RELIEF

HealthSelect®

Diphenhydramine HCl
Antihistamine

For Temporary Relief of:

- Itchy, Watery Eyes
- Itchy Throat
- Runny Nose
- Sneezing

For Ages 12 and Older
Alcohol Free

NET 4 FL OZ
(118 ML)

NDC 49743-3001-1